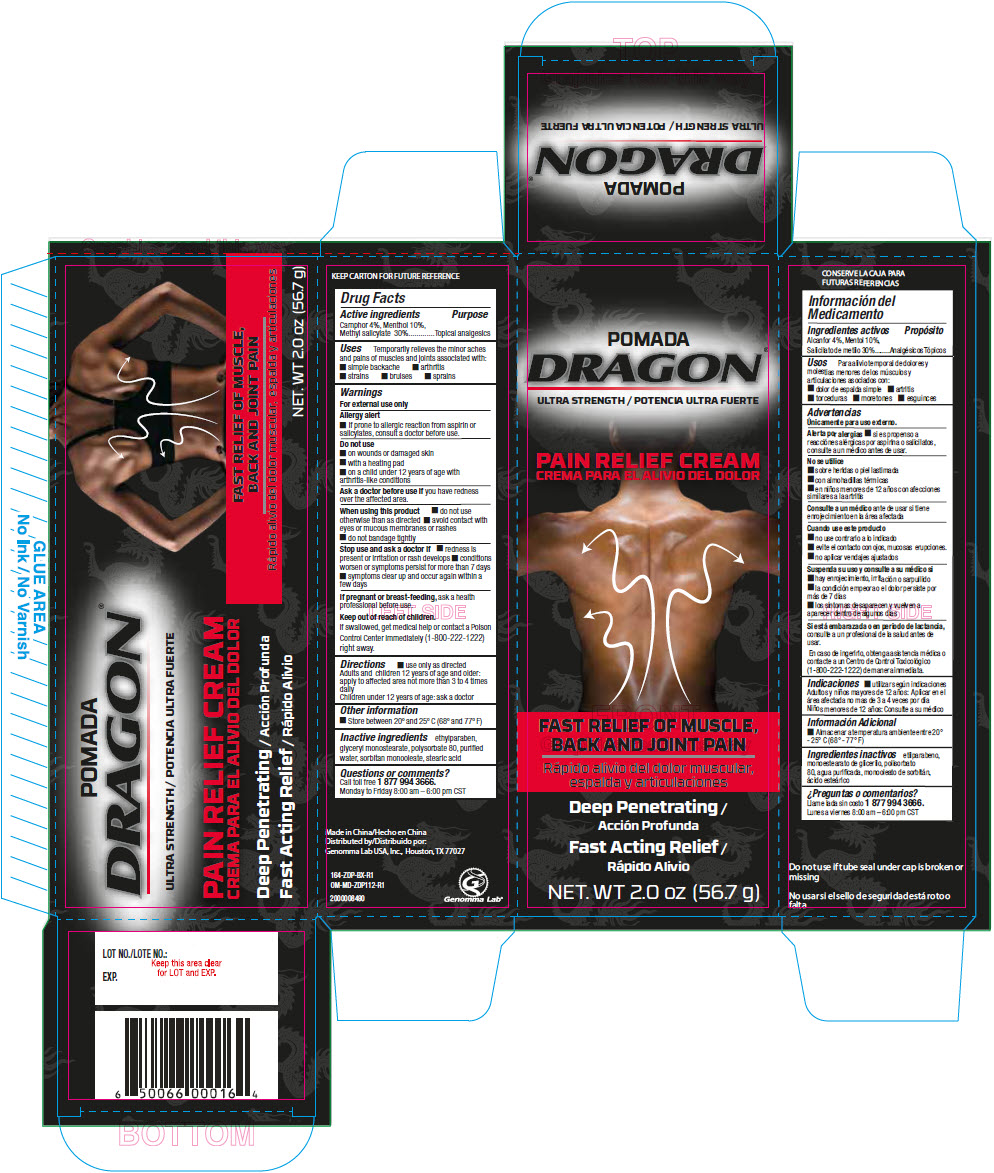 DRUG LABEL: Pomada Dragon Pain Relief
NDC: 50066-622 | Form: CREAM
Manufacturer: Genomma Lab USA
Category: otc | Type: HUMAN OTC DRUG LABEL
Date: 20250219

ACTIVE INGREDIENTS: MENTHOL, UNSPECIFIED FORM 100 mg/1 g; CAMPHOR (SYNTHETIC) 40 mg/1 g; METHYL SALICYLATE 300 mg/1 g
INACTIVE INGREDIENTS: water; glyceryl monostearate; polysorbate 80; sorbitan monooleate; stearic acid; ethylparaben

Pomada Dragon® Pain Relief Cream

Drug Facts

Active ingredients

Camphor 4%, Menthol 10%, Methyl salicylate 30%

Purpose

Topical analgesics

Uses

Temporarily relieves the minor aches and pains of muscles and joints associated with:

- simple backache
- arthritis
- strains
- bruises
- sprains

Warnings

For external use only

Allergy alert

- If prone to allergic reaction from aspirin or salicylates, consult a doctor before use.

Do not use

- on wounds or damaged skin
- with a heating pad
- on a child under 12 years of age with arthritis-like conditions

Ask a doctor before use if you have redness over the affected area.

When using this product

- do not use otherwise than as directed
- avoid contact with eyes or mucous membranes or rashes
- do not bandage tightly

Stop use and ask a doctor if

- redness is present or irritation or rash develops
- conditions worsen or symptoms persist for more than 7 days
- symptoms clear up and occur again within a few days

PREGNANCY OR BREAST FEEDING

If pregnant or breast-feeding, ask a health professional before use.

Keep out of reach of children.

If swallowed, get medical help or contact a Poison Control Center immediately (1-800-222-1222) right away.

Directions

- use only as directed

Adults and children 12 years of age and older: apply to affected area not more than 3 to 4 times daily

Children under 12 years of age: ask a doctor

Other information

- Store between 20° and 25° C (68° and 77° F)

Inactive ingredients

ethylparaben, glyceryl monostearate, polysorbate 80, purified water, sorbitan monooleate, stearic acid

Questions or comments?

Call toll free 1 877 994 3666.

Monday to Friday 8:00 am – 6:00 pm CST

Distributed by:
Genomma Lab USA, Inc., Houston, TX 77027

PRINCIPAL DISPLAY PANEL - 56.7 g Tube Carton

POMADA
DRAGON®

ULTRA STRENGTH

PAIN RELIEF CREAM

FAST RELIEF OF MUSCLE,
BACK AND JOINT PAIN

Deep Penetrating

Fast Acting Relief

NET. WT 2.0 oz (56.7 g)